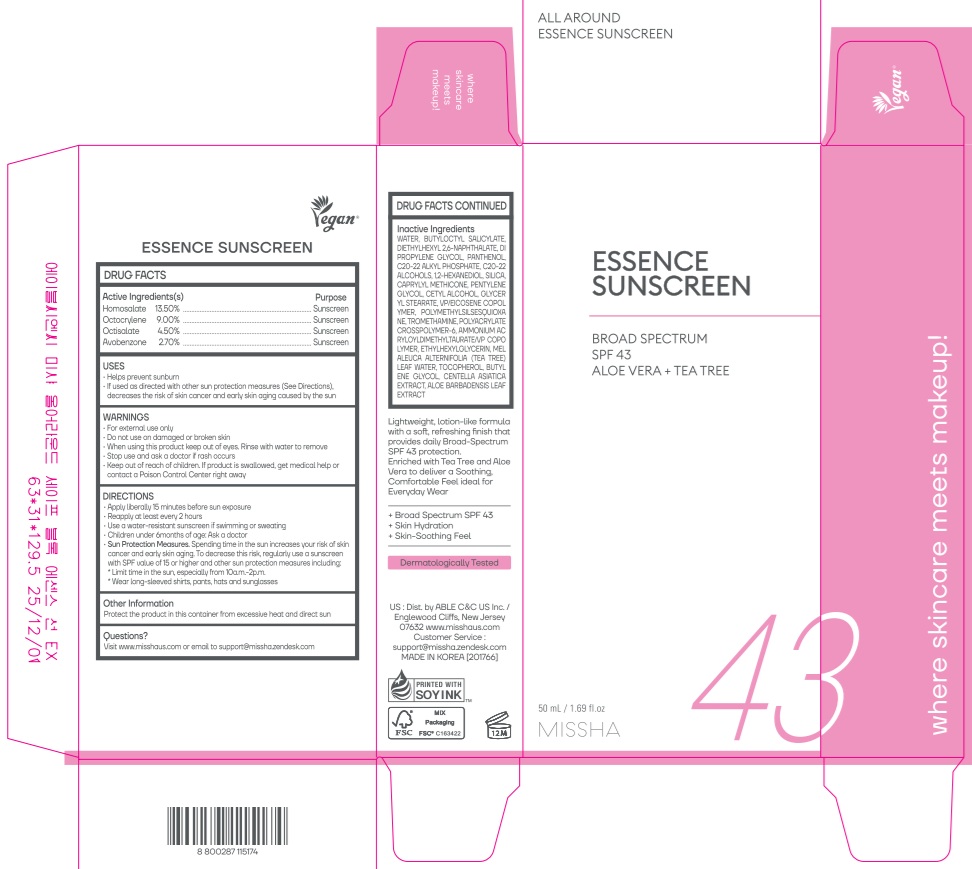 DRUG LABEL: MISSHA ALL AROUND ESSENCE SUNSCREEN
NDC: 13733-247 | Form: CREAM
Manufacturer: Able C&C Co., Ltd.
Category: otc | Type: HUMAN OTC DRUG LABEL
Date: 20260122

ACTIVE INGREDIENTS: HOMOSALATE 13.5 g/100 mL; AVOBENZONE 2.7 g/100 mL; OCTISALATE 4.5 g/100 mL; OCTOCRYLENE 9 g/100 mL
INACTIVE INGREDIENTS: WATER; CAPRYLYL METHICONE; SILICON DIOXIDE; PANTHENOL; BUTYLOCTYL SALICYLATE; C20-22 ALCOHOLS; DIPROPYLENE GLYCOL; C20-22 ALKYL PHOSPHATE; 1,2-HEXANEDIOL; DIETHYLHEXYL 2,6-NAPHTHALATE

MISSHA ALL AROUND ESSENCE SUNSCREEN

Active ingredient(s)

Homosalate 13.50%

Octocrylene 9.00%

Octisalate 4.50%

Avobenzone 2.70%

Purpose

Sunscreen

USES

■ Helps prevent sunburn

■ If used as directed with other sun protection measures (See Directions), decreases the risk of skin cancer and early skin aging caused by the sun

WARNINGS

■ For external use only

■ Do not use on damaged or broken skin

■ When using this product keep out of eyes. Rinse with water to remove

■ Stop use and ask a doctor if rash occurs

■ Keep out of reach of children. If product is swallowed, get medical help

or contact a Poison Control Center right away

Keep out of reach of children.

DIRECTIONS

■ Apply liberally 15 minutes before sun exposure

■ Reapply at least every 2 hours

■ Use a water-resistant sunscreen if swimming or sweating

■ Children under 6months of age: Ask a doctor

■ Sun Protection Measures. Spending time in the sun increases your risk of skin cancer and early skin aging. To decrease this risk, regularly use a sunscreen with SPF value of 15 or higher and other sun protection measures including:

* Limit time in the sun, especially from 10a.m.-2p.m.

* Wear long-sleeved shirts, pants, hats and sunglasses

Other Information

■ Protect the product in this container from excessive heat and direct sun

Questions?

■ Visit www.misshaus.com or email to support@missha.zendesk.com

Inactive ingredients

WATER, BUTYLOCTYL SALICYLATE, DIETHYLHEXYL 2,6-NAPHTHALATE, DIPROPYLENE GLYCOL, PANTHENOL, C20-22 ALKYL PHOSPHATE, C20-22 ALCOHOLS, 1,2-HEXANEDIOL, SILICA, CAPRYLYL METHICONE, PENTYLENE GLYCOL, CETYL ALCOHOL, GLYCERYL STEARATE, VP/EICOSENE COPOLYMER, POLYMETHYLSILSESQUIOXANE, TROMETHAMINE, POLYACRYLATE CROSSPOLYMER-6, AMMONIUM ACRYLOYLDIMETHYLTAURATE/VP COPOLYMER, ETHYLHEXYLGLYCERIN, MELALEUCA ALTERNIFOLIA (TEA TREE) LEAF WATER, TOCOPHEROL, BUTYLENE GLYCOL, CENTELLA ASIATICA EXTRACT, ALOE BARBADENSIS LEAF EXTRACT